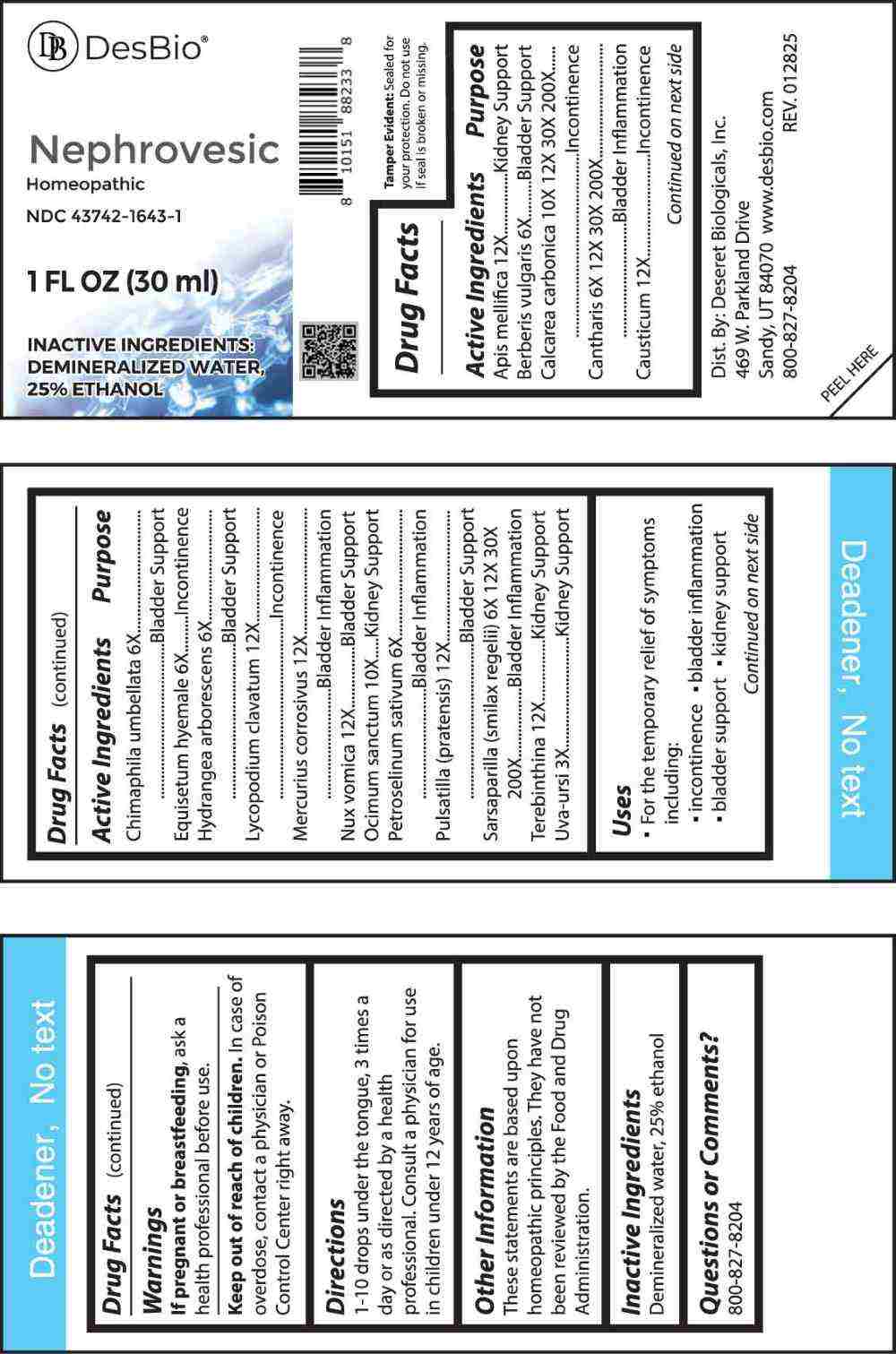 DRUG LABEL: Nephrovesic
NDC: 43742-1643 | Form: LIQUID
Manufacturer: Deseret Biologicals, Inc.
Category: homeopathic | Type: HUMAN OTC DRUG LABEL
Date: 20250429

ACTIVE INGREDIENTS: ARCTOSTAPHYLOS UVA-URSI LEAF 3 [hp_X]/1 mL; BERBERIS VULGARIS ROOT BARK 6 [hp_X]/1 mL; CHIMAPHILA UMBELLATA WHOLE 6 [hp_X]/1 mL; EQUISETUM HYEMALE WHOLE 6 [hp_X]/1 mL; HYDRANGEA ARBORESCENS ROOT 6 [hp_X]/1 mL; PETROSELINUM CRISPUM WHOLE 6 [hp_X]/1 mL; LYTTA VESICATORIA 6 [hp_X]/1 mL; SMILAX ORNATA ROOT 6 [hp_X]/1 mL; OCIMUM TENUIFLORUM TOP 10 [hp_X]/1 mL; OYSTER SHELL CALCIUM CARBONATE, CRUDE 10 [hp_X]/1 mL; APIS MELLIFERA 12 [hp_X]/1 mL; CAUSTICUM 12 [hp_X]/1 mL; LYCOPODIUM CLAVATUM SPORE 12 [hp_X]/1 mL; MERCURIC CHLORIDE 12 [hp_X]/1 mL; STRYCHNOS NUX-VOMICA SEED 12 [hp_X]/1 mL; PULSATILLA PRATENSIS WHOLE 12 [hp_X]/1 mL; TURPENTINE OIL 12 [hp_X]/1 mL
INACTIVE INGREDIENTS: WATER; ALCOHOL

DRUG FACTS:

ACTIVE INGREDIENTS:

Apis Mellifica 12X, Berberis Vulgaris 6X, Calcarea Carbonica 10X, 12X, 30X, 200X, Cantharis 6X, 12X, 30X, 200X, Causticum 12X, Chimaphila Umbellata 6X, Equisetum Hyemale 6X, Hydrangea Arborescens 6X, Lycopodium Clavatum 12X, Mercurius Corrosivus 12X, Nux Vomica 12X, Ocimum Sanctum 10X, Petroselinum Sativum 6X, Pulsatilla (Pratensis) 12X, Sarsaparilla (Smilax Regelii) 6X, 12X, 30X, 200X, Terebinthina 12X, Uva-Ursi 3X.

PURPOSES:

Apis Mellifica – Kidney Support, Berberis Vulgaris – Bladder Support, Calcarea Carbonica - Incontinence, Cantharis – Bladder Inflammation, Causticum - Incontinence, Chimaphila Umbellata – Bladder Support, Equisetum Hyemale - Incontinence, Hydrangea Arborescens – Bladder Support, Lycopodium Clavatum - Incontinence, Mercurius Corrosivus – Bladder Inflammation, Nux Vomica – Bladder Support, Ocimum Sanctum – Kidney Support, Petroselinum Sativum – Bladder Inflammation, Pulsatilla (Pratensis) – Bladder Support, Sarsaparilla (Smilax Regelii) – Bladder Inflammation, Terebinthina – Kidney Support, Uva-Ursi – Kidney Support.

USES:

• For the temporary relief of symptoms including:

• incontinence • bladder inflammation

• bladder support • kidney support

These statements are based upon homeopathic principles. They have not been reviewed by the Food and Drug Administration.

WARNINGS:

If pregnant or breastfeeding, ask a health professional before use.

Keep out of reach of children. In case of overdose, contact a physician or Poison Control Center right away.

Tamper Evident: Sealed for your protection. Do not use if seal is broken or missing.

KEEP OUT OF REACH OF CHILDREN:

In case of overdose, contact a physician or Poison Control Center right away.

DIRECTIONS:

1-10 drops under the tongue, 3 times a day or as directed by a health professional. Consult a physician for use in children under 12 years of age.

INACTIVE INGREDIENTS:

Demineralized water, 25% ethanol

QUESTIONS:

Dist. By: Deseret Biologicals, Inc.

469 W. Parkland Drive

Sandy, UT 84070

www.desbio.com

800-827-8204

PACKAGE LABEL DISPLAY:

Des Bio

Nephrovesic

Homeopathic

NDC 43742-1643-1

1 FL OZ (30 ml)